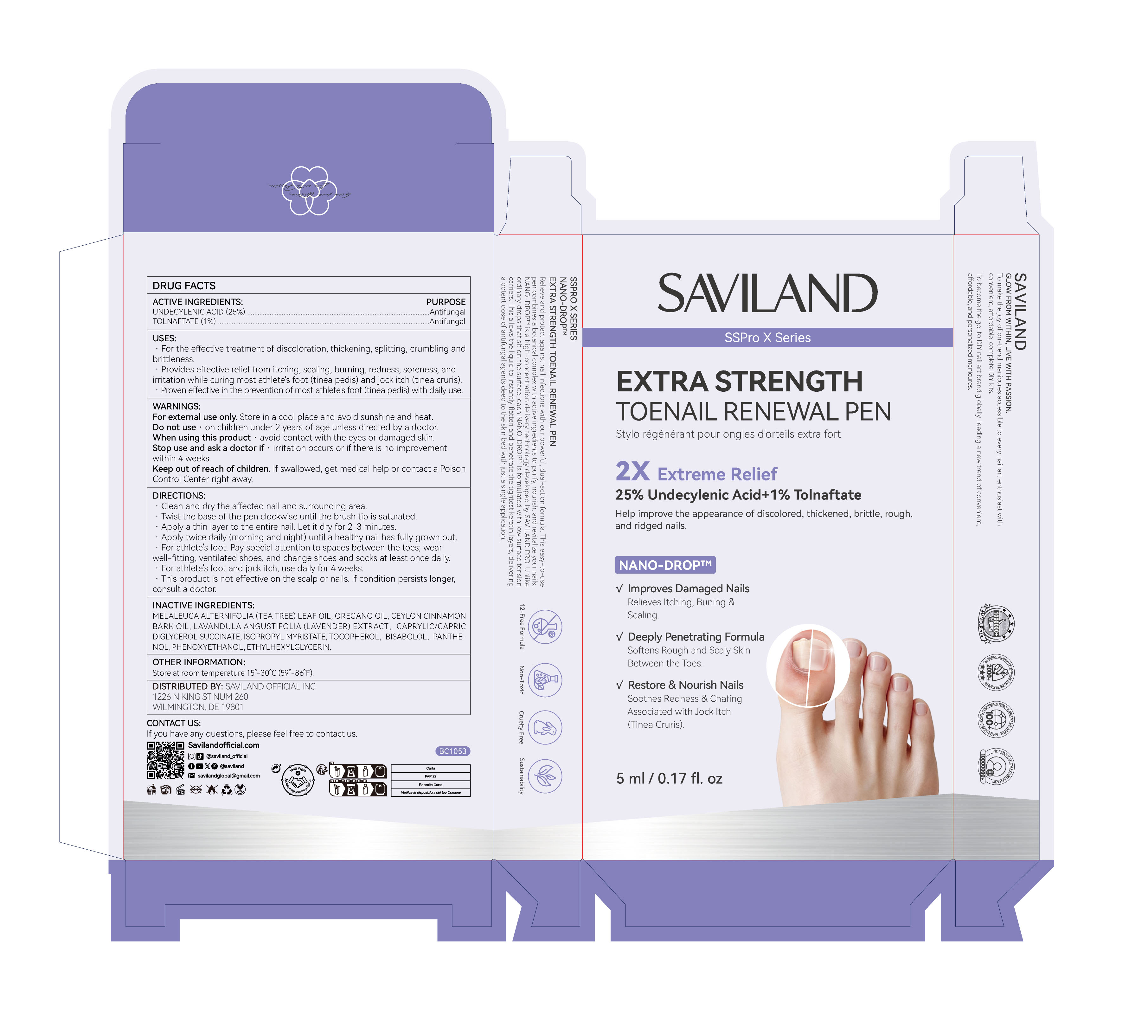 DRUG LABEL: Nail Fungus Treatment Pen
NDC: 85966-005 | Form: LIQUID
Manufacturer: GUANGZHOU SAWEILAN IMPORT & EXPORT TRADING CO., LTD
Category: otc | Type: HUMAN OTC DRUG LABEL
Date: 20260224

ACTIVE INGREDIENTS: UNDECYLENIC ACID 25 g/100 mL; TOLNAFTATE 1 g/100 mL
INACTIVE INGREDIENTS: OREGANO LEAF OIL; LAVANDULA ANGUSTIFOLIA FLOWERING TOP; BISABOLOL; PANTHENOL; CINNAMON BARK OIL; PHENOXYETHANOL; ISOPROPYL MYRISTATE; MELALEUCA ALTERNIFOLIA (TEA TREE) LEAF OIL; TOCOPHEROL; CAPRYLIC/CAPRIC/SUCCINIC TRIGLYCERIDE; ETHYLHEXYLGLYCERIN

85966-005 Nail Fungus Treatment Pen

ACTIVE INGREDIENT

UNDECYLENIC ACID 25%
TOLNAFTATE 1%

PURPOSE

Antifungal

INDICATIONS AND USAGE

. For the effective treatment of discoloration, thickening, splitting, crumbling and
brittleness.
.Provides effective relief from itching, scaling, burning, redness, soreness, andirritation while curing most athlete's foot (tinea pedis) and jock itch (tinea cruris).
Proven effective in the prevention of most athlete's foot (tinea pedis) with daily use

WARNINGS

For external use only, Store in a cool place and avoid sunshine and heat.

Do not use · on children under 2 years of age unless directed by a doctor.

When using this product · avoid contact with the eyes or damaged skin.

Stop use and ask a doctor if . irritation occurs or if there is no improvement within 4 weeks.

Keep out of reach of children. lf swallowed, get medical help or contact a Poison Control Center right away.

DOSAGE AND ADMINISTRATION

Clean and dry the affected nail and surrounding area.
Twist the base of the pen clockwise until the brush tip is saturated.
Apply a thin layer to the entire nail. Let it dry for 2-3 minutes.
Apply twice daily (morning and night) until a healthy nail has fully grown out.
For athletes foot: Pay special attention to spaces between the toes,wear well-fitting, ventilated shoes, and change shoes and socks at least once daily.
For athlete's foot and jock itch, use daily for 4 weeks..This product is not effective on the scalp or nails. lf condition persistslonger, consult a doctor.

INACTIVE INGREDIENT

MELALEUCA ALTERNIFOLIA (TEA TREE) LEAF OIL
OREGANO OIL
CEYLON CINNAMON BARK OIL
LAVANDULA ANGUSTIFOLIA (LAVENDER) EXTRACT
CAPRYLIC/CAPRIC DIGLYCEROL SUCCINATE
ISOPROPYL MYRISTATE
TOCOPHEROL
BISABOLOL
PANTHENOL
PHENOXYETHANOL
ETHYLHEXYLGLYCERIN